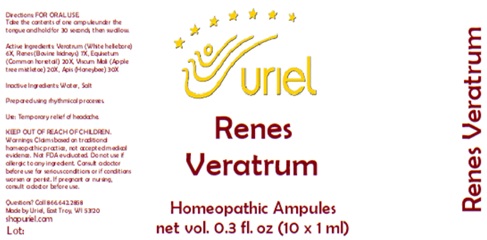 DRUG LABEL: Renes Veratrum
NDC: 48951-8132 | Form: LIQUID
Manufacturer: Uriel Pharmacy Inc.
Category: homeopathic | Type: HUMAN OTC DRUG LABEL
Date: 20241220

ACTIVE INGREDIENTS: VERATRUM ALBUM ROOT 6 [hp_X]/1 mL; PORK KIDNEY 7 [hp_X]/1 mL; EQUISETUM ARVENSE TOP 20 [hp_X]/1 mL; VISCUM ALBUM FRUITING TOP 20 [hp_X]/1 mL; APIS MELLIFERA 30 [hp_X]/1 mL
INACTIVE INGREDIENTS: WATER; SODIUM CHLORIDE

Renes Veratrum

INDICATIONS AND USAGE

Directions: FOR ORAL USE.

DOSAGE AND ADMINISTRATION

Take the contents of one ampule under the tongue and hold for 30 seconds, then swallow.

ACTIVE INGREDIENT

Active Ingredients: Veratrum (White hellebore) 6X, Renes (Bovine kidneys) 7X, Equisetum (Common horsetail) 20X, Viscum Mali (Apple tree mistletoe) 20X, Apis (Honeybee) 30X

Inactive Ingredients: Water, Salt

Prepared using rhythmical processes.

PURPOSE

Use: Temporary relief of headache.

KEEP OUT OF REACH OF CHILDREN.

WARNINGS

Warnings: Claims based on traditional homeopathic practice, not accepted medical evidence. Not FDA evaluated. Do not use if allergic to any ingredient. Consult a doctor before use for serious conditions or if conditions worsen or persist. If pregnant or nursing, consult a doctor before use.

QUESTIONS

Questions? Call 866.642.2858 Made by Uriel, East Troy, WI 53120 www.urielpharmacy.com